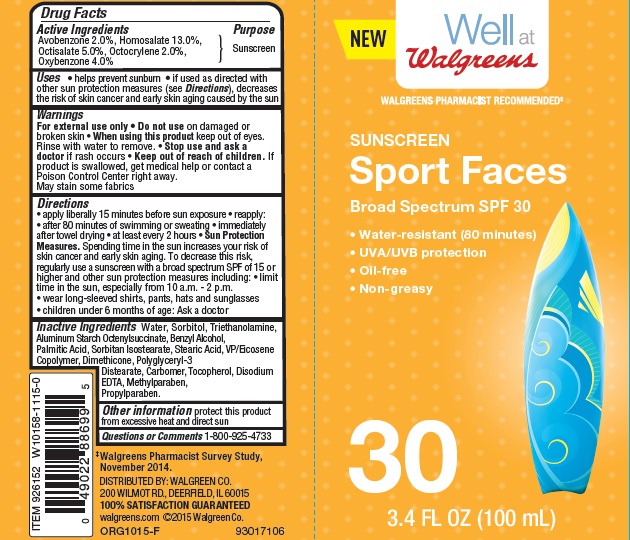 DRUG LABEL: Walgreens Sport Faces SPF 30
NDC: 0363-3890 | Form: LOTION
Manufacturer: Walgreen Co.
Category: otc | Type: HUMAN OTC DRUG LABEL
Date: 20160608

ACTIVE INGREDIENTS: AVOBENZONE 2 g/100 g; HOMOSALATE 13 g/100 g; OCTOCRYLENE 1 g/100 g; OCTISALATE 5 g/100 g; OXYBENZONE 4 g/100 g
INACTIVE INGREDIENTS: WATER; SORBITOL; TROLAMINE; ALUMINUM STARCH OCTENYLSUCCINATE; BENZYL ALCOHOL; PALMITIC ACID; SORBITAN ISOSTEARATE; STEARIC ACID; DIMETHICONE; POLYGLYCERYL-3 DISTEARATE; CARBOXYPOLYMETHYLENE; TOCOPHEROL; EDETATE DISODIUM; METHYLPARABEN; PROPYLPARABEN

Drug Facts

Active Ingredients

Avobenzone 2.0%, Homosalate 13.0%, Octisalate 5.0%, Octocrylene 2.0%, Oxybenzone 4.0%

Purpose

Sunscreen

Uses

- helps prevent sunburn
- if used as directed with other sun protection measures (see Directions), decreases the risk of skin cancer and early skin aging caused by the sun

Warnings

For external use only

Do not use

on damaged or broken skin

When using this product

keep out of eyes. Rinse with water to remove.

Stop use and ask a doctor

if rash occurs

Keep out of reach of children.

If product is swallowed, get medical help or contact a Poison Control Center right away.

- May stain some fabrics

Directions

- apply liberally 15 minutes before sun exposure
- reapply:
- after 80 minutes of swimming or sweating
- immediately after towel drying
- at least every 2 hours
- Sun Protection Measures: Spending time in the sun increases your risk of skin cancer and early skin aging. To decrease this risk, regularly use a sunscreen with a broad spectrum SPF of 15 or higher and other sun protection measures including:
- limit time in the sun, especially from 10 a.m. to 2 p.m.
- wear long-sleeved shirts, pants, hats, and sunglasses
- children under 6 months: Ask a doctor

Inactive Ingredients

Water, Sorbitol, Triethanolamine, Aluminum Starch Octenylsuccinate, Benzyl Alcohol, Palmitic Acid, Sorbitan Isostearate, Stearic Acid, VP/Eicosene Copolymer, Dimethicone, Polyglyceryl-3 Distearate, Carbomer, Tocopherol, Disodium EDTA, Methylparaben, Propylparaben.

Other information

• protect this product from excessive heat and direct sun

Questions or comments

1-800-925-4733

Principle Display Label

NDC: 0363-3890-22

New

Well at Walgreens

Walgreens Pharmacist Recommended*

Sunscreen

Sport Faces

Broad Spectrum SPF 30

Water Resistant (80 minutes)

UVA/UVB protection

Oil-free

Non-greasy

30

3.4 FL OZ (100 mL)